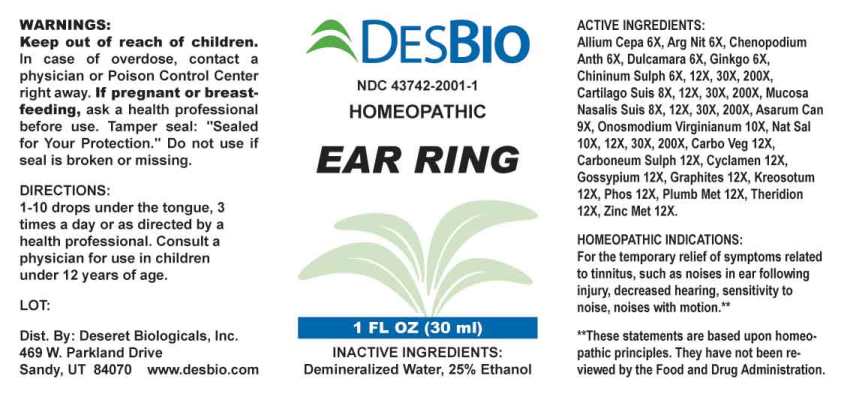 DRUG LABEL: Ear Ring
NDC: 43742-2001 | Form: LIQUID
Manufacturer: Deseret Biologicals, Inc.
Category: homeopathic | Type: HUMAN OTC DRUG LABEL
Date: 20240508

ACTIVE INGREDIENTS: ONION 6 [hp_X]/1 mL; SILVER NITRATE 6 [hp_X]/1 mL; DYSPHANIA AMBROSIOIDES WHOLE 6 [hp_X]/1 mL; SOLANUM DULCAMARA TOP 6 [hp_X]/1 mL; GINKGO 6 [hp_X]/1 mL; QUININE SULFATE 6 [hp_X]/1 mL; SUS SCROFA CARTILAGE 8 [hp_X]/1 mL; SUS SCROFA NASAL MUCOSA 8 [hp_X]/1 mL; ASARUM CANADENSE ROOT 9 [hp_X]/1 mL; ONOSMODIUM VIRGINIANUM 10 [hp_X]/1 mL; SODIUM SALICYLATE 10 [hp_X]/1 mL; ACTIVATED CHARCOAL 12 [hp_X]/1 mL; CARBON DISULFIDE 12 [hp_X]/1 mL; CYCLAMEN PURPURASCENS TUBER 12 [hp_X]/1 mL; GOSSYPIUM HERBACEUM ROOT BARK 12 [hp_X]/1 mL; GRAPHITE 12 [hp_X]/1 mL; WOOD CREOSOTE 12 [hp_X]/1 mL; PHOSPHORUS 12 [hp_X]/1 mL; LEAD 12 [hp_X]/1 mL; THERIDION CURASSAVICUM 12 [hp_X]/1 mL; ZINC 12 [hp_X]/1 mL
INACTIVE INGREDIENTS: WATER; ALCOHOL

DRUG FACTS:

ACTIVE INGREDIENTS:

Allium Cepa 6X, Argentum Nitricum 6X, Chenopodium Anthelminticum 6X, Dulcamara 6X, Ginkgo Biloba 6X, Chininum Sulphuricum 6X, 12X, 30X, 200X, Cartilago Suis 8X, 12X, 30X, 200X, Mucosa Nasalis Suis 8X, 12X, 30X, 200X, Asarum Canadense 9X, Onosmodium Virginianum 10X, Natrum Salicylicum 10X, 12X, 30X, 200X, Carbo Vegetabilis 12X, Carboneum Sulphuratum 12X, Cyclamen Europaeum 12X, Gossypium Herbaceum 12X, Graphites 12X, Kreosotum 12X, Phosphorus 12X, Plumbum Metallicum 12X, Theridion 12X, Zincum Metallicum 12X.

HOMEOPATHIC INDICATIONS:

For the temporary relief of symptoms related to tinnitus, such as noises in ear following injury, decreased hearing, sensitivity to noise, noises with motion .**

**These statements are based upon homeopathic principles. They have not been reviewed by the Food and Drug Administration.

WARNINGS:

Keep out of reach of children. In case of overdose, contact a physician or Poison Control Center right away.

If pregnant or breast-feeding, ask a health professional before use.

Tamper seal: "Sealed for Your Protection." Do not use if seal is broken or missing.

Keep out of reach of children. In case of overdose, contact a physician or Poison Control Center right away.

DIRECTIONS:

1-10 drops under the tongue, 3 times a day or as directed by a health professional. Consult a physician for use in children under 12 years of age.

HOMEOPATHIC INDICATIONS:

For the temporary relief of symptoms related to tinnitus, such as noises in ear following injury, decreased hearing, sensitivity to noise, noises with motion .**

**These statements are based upon homeopathic principles. They have not been reviewed by the Food and Drug Administration.

INACTIVE INGREDIENTS:

Demineralized Water, 25% Ethanol

QUESTIONS:

Dist. By: Deseret Biologicals, Inc.

469 W. Parkland Drive

Sandy, UT 84070 www.desbio.com

PACKAGE LABEL DISPLAY:

DESBIO

NDC 43742-2001-1

HOMEOPATHIC

EAR RING

1 FL OZ (30 ml)